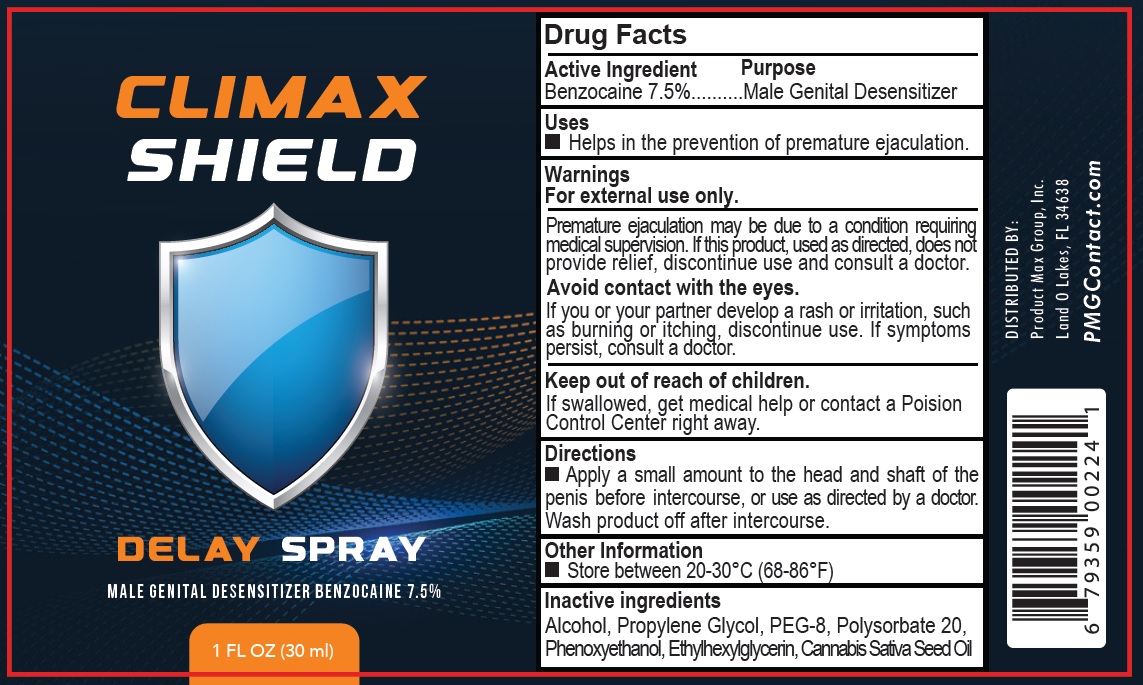 DRUG LABEL: Climax Shield Delay
NDC: 70742-598 | Form: LIQUID
Manufacturer: PRODUCT MAX GROUP INC
Category: otc | Type: HUMAN OTC DRUG LABEL
Date: 20250505

ACTIVE INGREDIENTS: BENZOCAINE 75 mg/1 mL
INACTIVE INGREDIENTS: ALCOHOL; PROPYLENE GLYCOL; POLYETHYLENE GLYCOL 400; POLYSORBATE 20; PHENOXYETHANOL; ETHYLHEXYLGLYCERIN; CANNABIS SATIVA SEED OIL

Climax Shield Delay Spray

Active Ingredient

Benzocaine 7.5%

Purpose

Male Genital Desensitizer

Uses

- Helps in the prevention of premature ejaculation.

Warnings

For external use only.

Premature ejaculation may be due to a condition requiring medical supervision. If this product, used as directed, does not provide relief, discontinue use and consult a doctor.

Avoid contact with the eyes.

If you or your partner develop a rash or irritation, such as burning or itching, discontinue use. If symptoms persist, consult a doctor.

Keep out of reach of children.

If swallowed, get medical help or contact a Poison Control Center right away.

Directions

- Apply a small amount to the head and shaft of the penis before intercourse, or use as directed by a doctor. Wash product off after intercourse.

Other Information

- Store between 20-30°C (68-86°F)

Inactive ingredients

Alcohol, Propylene Glycol, PEG-8, Polysorbate 20, Phenoxyethanol, Ethylhexylglycerin, Cannabis Sativa Seed Oil